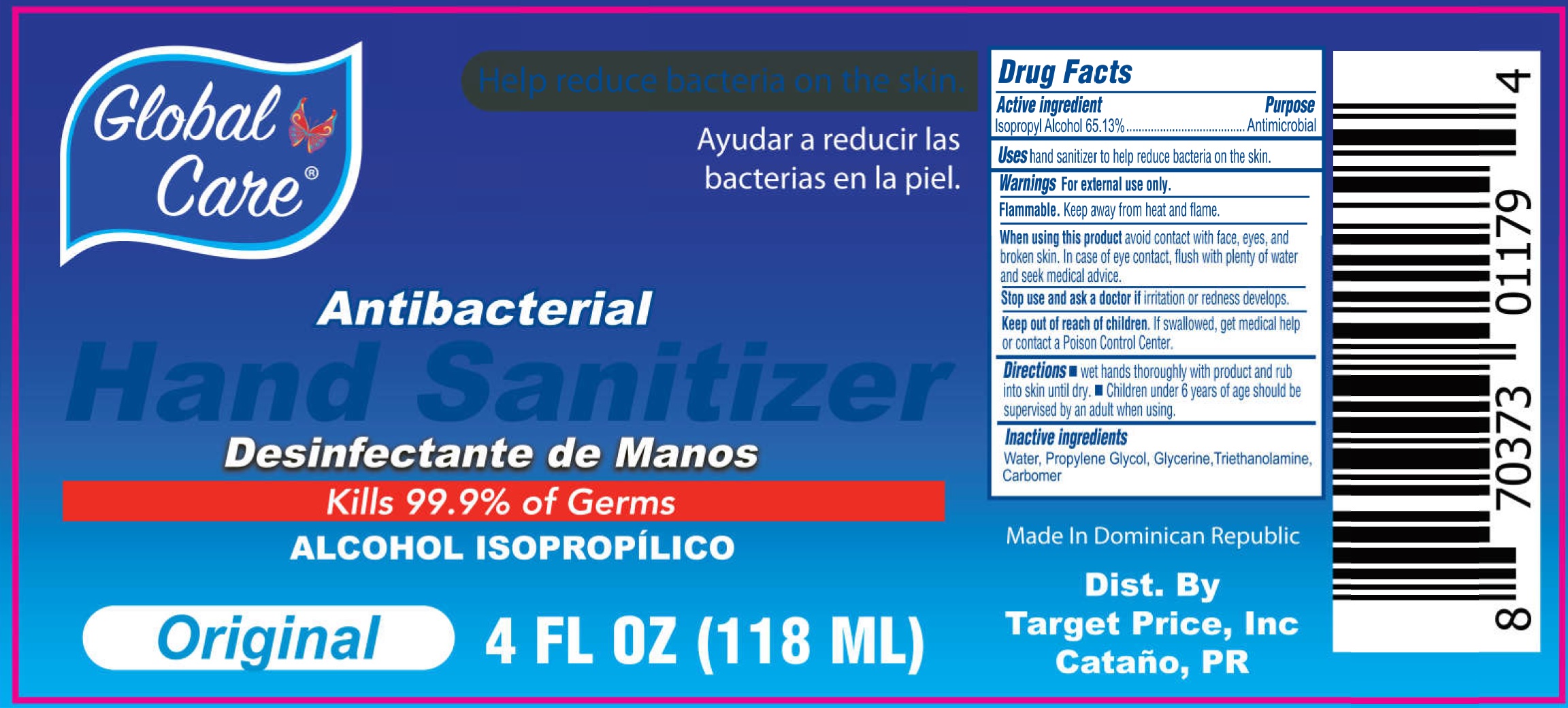 DRUG LABEL: HAND SANITIZER GLOBAL CARE
NDC: 72146-029 | Form: GEL
Manufacturer: TARGET PRICE INC.
Category: otc | Type: HUMAN OTC DRUG LABEL
Date: 20200911

ACTIVE INGREDIENTS: ALCOHOL 0.7 mL/1 mL
INACTIVE INGREDIENTS: WATER; PROPYLENE GLYCOL; GLYCERIN; TROLAMINE; CARBOMER HOMOPOLYMER, UNSPECIFIED TYPE

HAND SANITIZER GLOBAL CARE

Active ingredient

Isopropyl Alcohol 70%

Purpose

Antimicrobial

Uses

hand sanitizer to help reduce bacteria on the skin.

Warnings

For external use only.

Flammable. Keep away from heat and flame.

When using this product

avoid contact with face, eyes, and broken skin. In case of eye contact, flush with plenty of water and seek medical advice.

Stop use and ask a doctor if

irritation or redness develops.

Keep out of reach of children.

If swallowed, get medical help or contact a Poison Control Center.

Directions

- wet hands thoroughly with product and rub into skin until dry.
- Children under 6 years of age should be supervised by an adult when using.

Inactive ingredients

Water, Propylene Glycol, Glycerine, Triethanolamine, Carbomer